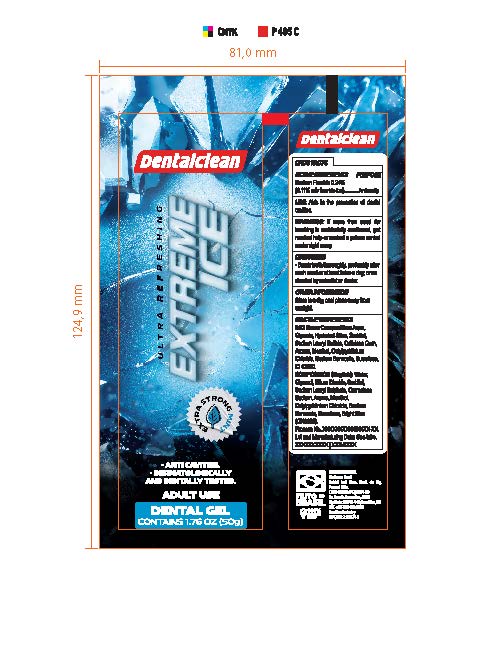 DRUG LABEL: Dentalclean Ultra Refreshing Extreme Ice Dental Gel
NDC: 84035-001 | Form: PASTE, DENTIFRICE
Manufacturer: Rabbit Indústria e Comércio de Produtos de Higiene Pessoal Ltda
Category: otc | Type: HUMAN OTC DRUG LABEL
Date: 20240326

ACTIVE INGREDIENTS: SODIUM FLUORIDE 2.4 mg/1 g
INACTIVE INGREDIENTS: SUCRALOSE; CETYLPYRIDINIUM CHLORIDE ANHYDROUS; WATER; HYDRATED SILICA; SORBITOL; SODIUM LAURYL SULFATE; MENTHOL; CARBOXYMETHYLCELLULOSE; GLYCERIN; SODIUM BENZOATE; FD&C BLUE NO. 1

Dentalclean Ultra Refreshing Extreme Ice Dental Gel

ACTIVE INGREDIENT

Sodium fluoride 0.24%

PURPOSE

Anticavity

INDICATIONS AND USAGE

Useaids in the prevention of dental cavities

WARNINGS

WARNINGS: If more than used for brushing is accidentally swallowed, get medical help or contact poison control center right away.

Directions

- Brush teeth thoroughly, preferably after each meal or at least twice a day, or as directed by a dentist or doctor

INACTIVE INGREDIENT

Water, Glycerol, Silium Dioxide, Sorbitol, Sodium Lauryl Sulphate, Carmelose Sodium, Aroma, Menthol, Cetylpyridinium Chloride, Sodium Benzoate, Sucralose, Bright Blue (CI42090)

OTHER SAFETY INFORMATION

Store in a dry, cool place away from sunlight.

Keep out of reach of children